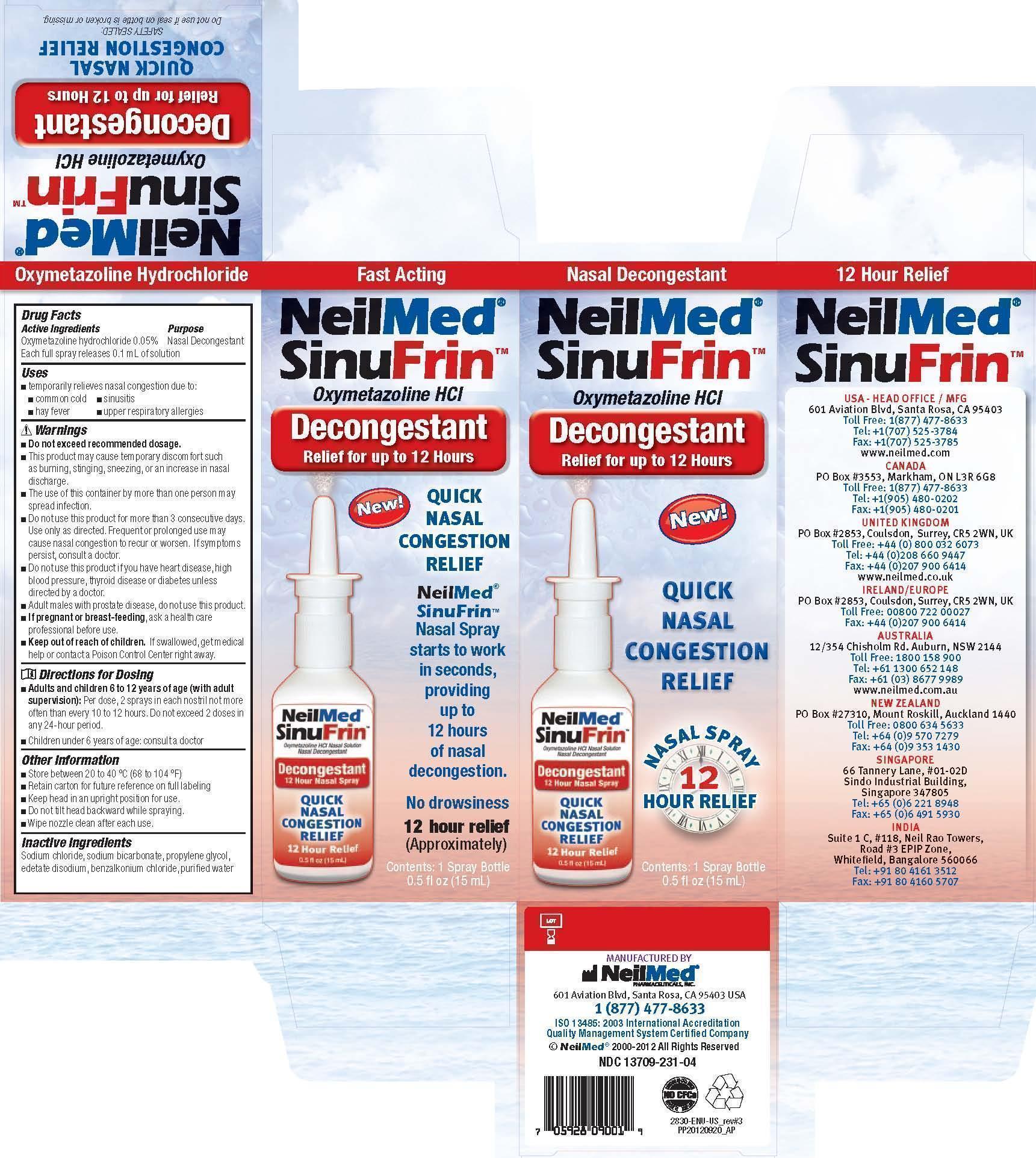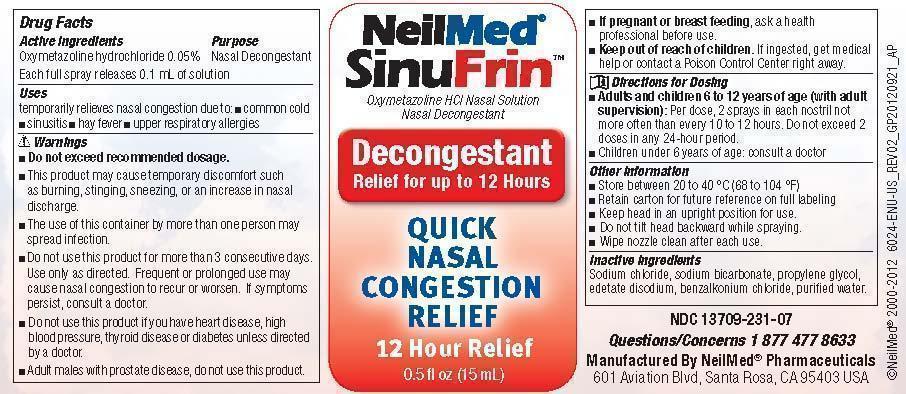 DRUG LABEL: SinuFrin
NDC: 13709-231 | Form: SPRAY
Manufacturer: NeilMed Pharmaceuticals Inc
Category: otc | Type: HUMAN OTC DRUG LABEL
Date: 20240111

ACTIVE INGREDIENTS: OXYMETAZOLINE HYDROCHLORIDE 7.5 mg/15 mL
INACTIVE INGREDIENTS: SODIUM CHLORIDE; SODIUM BICARBONATE; PROPYLENE GLYCOL; EDETATE DISODIUM; BENZALKONIUM CHLORIDE; WATER

Drug Facts

Active Ingredients

0.05% Oxymetazoline Hydrochloride

Uses

temporarily relieves nasal congestion due to: common cold n sinusitis, hay fever, upper respiratory allergies

Warnings

Do not exceed recommended dosage. This product may cause temporary discomfort such as burning, stinging, sneezing, or an increase in nasal discharge. The use of this container by more than one person may spread infection.

Warnings

Do not use this product for more than 3 consecutive days. Use only as directed. Frequent or prolonged use may cause nasal congestion to recur or worsen. If symptoms persist, consult a doctor. Do not use this product if you have heart disease, high blood pressure, thyroid disease or diabetes unless directed by a doctor.

Directions for Dosing

Adults and children 6 to 12 years of age (with adult supervision): Per dose, 2 sprays in each nostril not more often than every 10 to 12 hours. Do not exceed 2 doses in any 24-hour period. Children under 6 years of age: consult a doctor.

Other Information

Store between 20 to 40 °C (68 to 104 °F)
Retain carton for future reference on full labeling

Warnings

Keep out of reach of children. If swallowed, get medical help or contact a Poison Control Center right away.

Warnings

Do not use this product for more than 3 consecutive days. Use only as directed. Frequent or prolonged use may
cause nasal congestion to recur or worsen. If symptoms persist, consult a doctor. Do not use this product if you have heart disease, high
blood pressure, thyroid disease or diabetes unless directed by a doctor. Adult males with prostate disease, do not use this product.

Other Information

Keep head in an upright position for use. Do not tilt head backward while spraying. Wipe nozzle clean after each use.

Warnings

Stop using this product for more than 3 consecutive days. Stop and ask your doctor if symptoms of nasal congestion persist after using 3 consecutive days.

Warnings

If pregnant or breast-feeding, ask a health care professional before use.

Uses

temporarily relieves nasal congestion due to: common cold n sinusitis, hay fever, upper respiratory allergies.

Inactive Ingredients

Sodium chloride, sodium bicarbonate, propylene glycol, edetate disodium, benzalkonium chloride, purified water